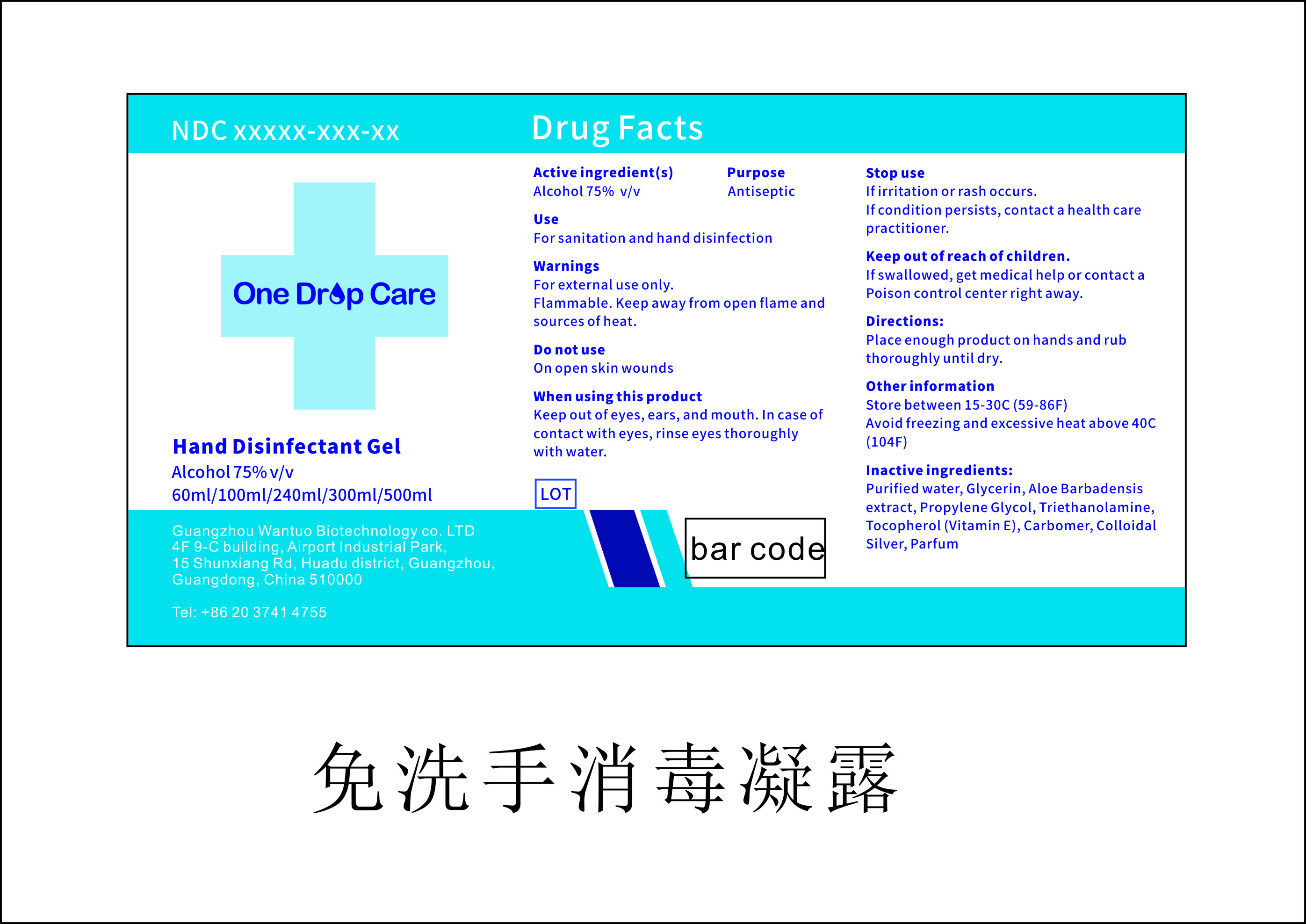 DRUG LABEL: One Drop Care Hand Disinfectant
NDC: 75226-004 | Form: GEL
Manufacturer: Guangzhou Wantuo Biotechnology Co. LTD
Category: otc | Type: HUMAN OTC DRUG LABEL
Date: 20200417

ACTIVE INGREDIENTS: ALCOHOL 75 mL/100 mL
INACTIVE INGREDIENTS: WATER; GLYCERIN; ALOE ANDONGENSIS WHOLE; PROPYLENE GLYCOL; TRIETHANOLAMINE SULFATE; TOCOPHEROL; CARBOMER 940

NA

Active Ingredient(s)

Alcohol 75%

Purpose

Antiseptic

Use

Sterilizing and cleaning hands, skin, and daily necessites

Warnings

For external use only. Flammable. Keep away from open flame and sources of heat

Do not use on open skin wounds

When using this product keep out of eyes, ears, and mouth. In case of contact with eyes, rinse eyes thoroughly with water.

Stop use if irritation or rash occurs. If condition persists contact a healthcare pratitioner

Keep out of reach of children. If swallowed, get medical help or contact a Poison Control Center right away.

Directions

Apply to intended area as needed

Other information

- Store between 15-30C (59-86F)
- Avoid freezing and excessive heat above 40C (104F)

Inactive ingredients

Purified Water, Glycerin, Aloe Barbadensis Extract, Propylene Glycerol, Triethanolamine, Tocopherol (Vitamin E), Carbomer, Colloidal Silver, Parfum